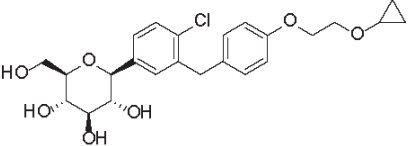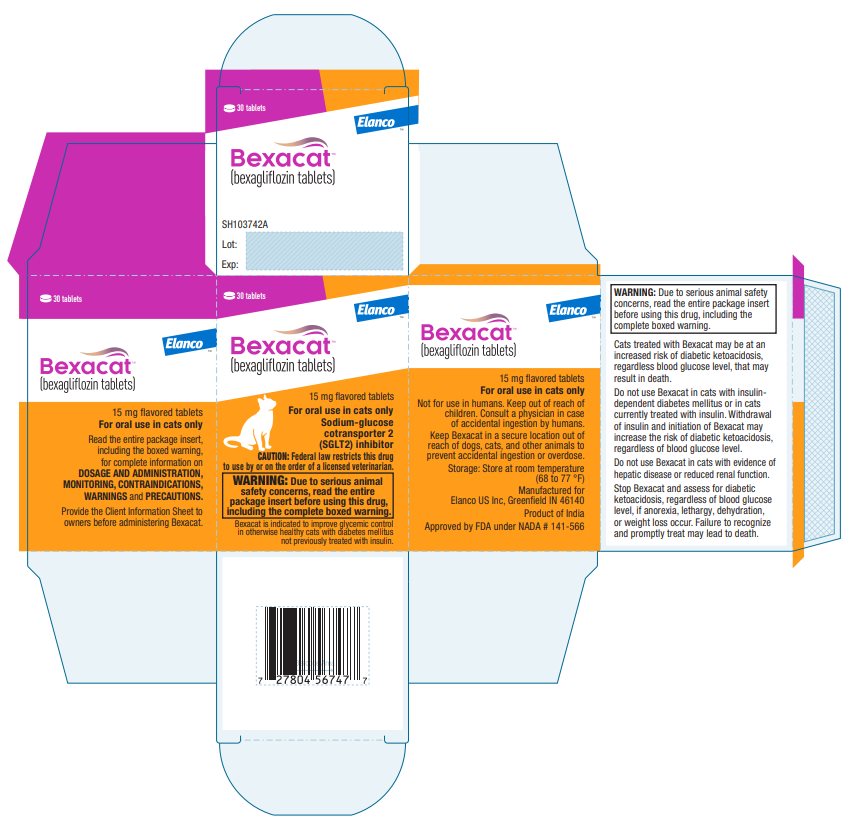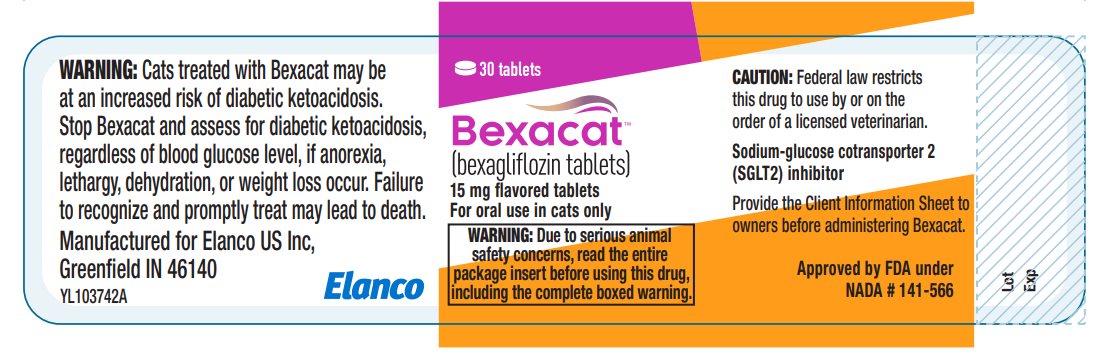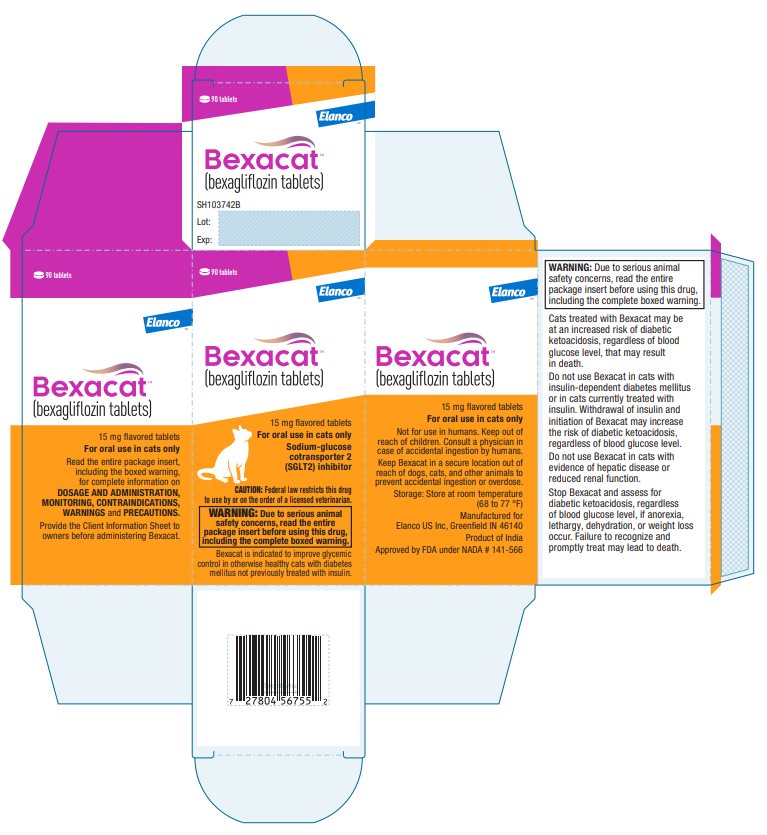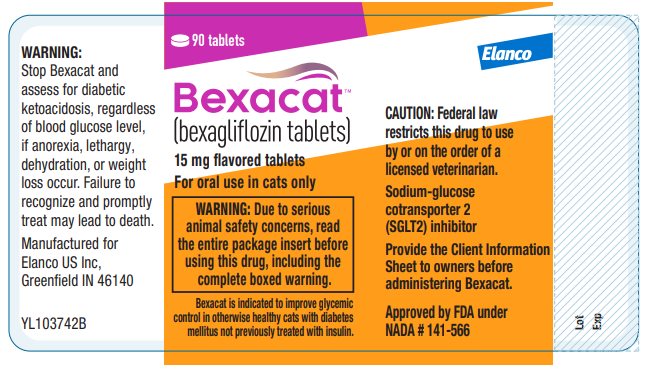 DRUG LABEL: Bexacat
NDC: 58198-5315 | Form: TABLET
Manufacturer: Elanco US Inc.
Category: animal | Type: PRESCRIPTION ANIMAL DRUG LABEL
Date: 20230125

ACTIVE INGREDIENTS: BEXAGLIFLOZIN 15 mg/1 1

ElancoTM
BexacatTM
(bexagliflozin tablets)

15 mg flavored tablets
For oral use in cats only
Sodium-glucose cotransporter 2 (SGLT2) inhibitor

CAUTION

Federal law restricts this drug to use by or on the order of a licensed veterinarian.

WARNING: DIABETIC KETOACIDOSIS/EUGLYCEMIC DIABETIC KETOACIDOSIS

- Cats treated with Bexacat may be at an increased risk of diabetic ketoacidosis or euglycemic diabetic ketoacidosis (see Adverse Reactions). As diabetic ketoacidosis and euglycemic diabetic ketoacidosis in cats treated with Bexacat may result in death, development of these conditions should be treated promptly, including insulin administration and discontinuation of Bexacat (see Monitoring).
- Due to the risk of developing diabetic ketoacidosis or euglycemic diabetic ketoacidosis, do not use Bexacat in cats with diabetes mellitus who have previously been treated with insulin, who are receiving insulin, or in cats with insulin-dependent diabetes mellitus (see Contraindications).
- Bexacat should not be initiated in cats with anorexia, dehydration or lethargy at the time of diagnosis of diabetes mellitus or without appropriate screening tests (see Animal Safety Warnings).

DESCRIPTION

Bexacat (bexagliflozin tablets) are flavored pentagonal, 10 mm, speckled white, brown, or tan biconvex with a characteristic odor. The empirical formula is C24H29ClO7 and the molecular weight is 464.94 g/mol. The chemical name is (2S,3R,4R,5S,6R)-2-(4-chloro-3-(4-(2-cyclopropoxyethoxy)benzyl)phenyl)-6-(hydroxymethyl)tetrahydro-2H-pyran-3,4,5-triol. The chemical structure of bexagliflozin is:

INDICATION

Bexacat is indicated to improve glycemic control in otherwise healthy cats with diabetes mellitus not previously treated with insulin.

DOSAGE AND ADMINISTRATION

Always provide the Client Information Sheet with the prescription.

Dosing Instructions

Administer one tablet by mouth to cats weighing 6.6 lbs (3.0 kg) or greater once daily, at approximately the same time each day, with or without food, and regardless of blood glucose level.

Monitoring

- Sudden onset of hyporexia/anorexia, lethargy, dehydration, or weight loss in cats receiving Bexacat should prompt immediate discontinuation of Bexacat and assessment for diabetic ketoacidosis, regardless of blood glucose level.
- During treatment with Bexacat, blood glucose, fructosamine, serum β-hydroxybutyrate (BHBA), serum feline pancreas-specific lipase (fPL), liver parameters, serum cholesterol and triglycerides; and body weight and clinical signs should be routinely monitored.
  - Increasing or persistently elevated feline pancreas-specific lipase or liver parameters should prompt further evaluation for pancreatitis and/or hepatic disease and consideration for discontinuing Bexacat.
  - BHBA is the predominate ketoacid in diabetic ketoacidosis. Bexacat should be discontinued if a notable reduction in BHBA is not observed after initiation of Bexacat, or if BHBA persistently rises after an initial reduction.
  - Cats with increasing or persistently elevated cholesterol and triglyceride levels may be at an increased risk for developing diabetic ketoacidosis or euglycemic diabetic ketoacidosis.
  - Bexacat should be discontinued if poor glycemic control, as described below, develops.
- During the first 8 weeks after initiation of Bexacat, assessment of glycemic control and clinical improvement should be evaluated.
  - A physical examination, an 8-hour blood glucose curve, serum fructosamine and body weight should be assessed at 2, 4 and 8 weeks.
  - Cats demonstrating poor glycemic control, including weight loss, an average blood glucose concentration from an 8-hour blood glucose curve ≥ 250 mg/dL, and/or a fructosamine indicating poor glycemic control should be closely monitored.
  - Bexacat should be discontinued, and initiation of insulin considered in cats demonstrating poor glycemic control, as described above, at 8 weeks.
- Cats may present with diabetic ketoacidosis and a normal blood glucose concentration (euglycemic diabetic ketoacidosis). Delay in recognition and treatment of diabetic ketoacidosis and euglycemic diabetic ketoacidosis may result in increased morbidity and mortality.
- Development of diabetic ketoacidosis and euglycemic diabetic ketoacidosis requires the following actions:
  - Discontinuation of Bexacat
  - Prompt initiation of insulin therapy
  - Administration of dextrose or other carbohydrate source, regardless of blood glucose concentration
  - Appropriate nutritional support should be promptly initiated to prevent or treat hepatic lipidosis.

For more information refer to CONTRAINDICATIONS and WARNINGS.

CONTRAINDICATIONS

- Do not use Bexacat in cats with diabetes mellitus who have previously been treated with insulin, who are receiving insulin, or in cats with insulin-dependent diabetes mellitus. The use of Bexacat in cats with insulin-dependent diabetes mellitus, or the withdrawal of insulin and initiation of Bexacat, is associated with an increased risk of diabetic ketoacidosis or euglycemic diabetic ketoacidosis and death.
- Due to risk of severe adverse reactions, do not use Bexacat in cats with evidence of hepatic disease or reduced renal function.

WARNINGS

User Safety Warnings

Not for use in humans. Keep out of reach of children. Consult a physician in case of accidental ingestion by humans.

Animal Safety Warnings

- Bexacat should not be initiated in cats with:
  - Anorexia, dehydration, or lethargy at the time of diagnosis of diabetes mellitus, as it may indicate the presence of other concurrent disease and increase the risk of diabetic ketoacidosis.
  - An fPL level > 5.3 mcg/L, diagnostic imaging consistent with pancreatitis, a history of pancreatitis, or current clinical signs suggestive of pancreatitis.
  - Laboratory values consistent with diabetic ketoacidosis, including elevated urine or serum ketones, and metabolic acidosis (high anion gap, or decreased bicarbonate, pH, or partial pressure carbon dioxide [PaCO2] levels).
  - A BHBA > 37 mg/dL, or if BHBA is > 25 mg/dL and the cat has a history of renal disease or metabolic acidosis.
- Persistent plasma bexagliflozin concentrations and reduced clearance of Bexacat, represented as the presence of plasma half-lives in excess of 24 hours, may result in prolonged clinical effects such as glucosuria and/or euglycemia despite discontinuation of Bexacat in some cats with hepatic disease and/or reduced renal function, including cats with clinically undetectable disease at the time of Bexacat initiation. Reduced clearance of Bexacat may contribute to persistent glucosuria, resulting in an osmotic diuresis and dehydration that requires appropriate hydration support. These cats may require hospitalization, which may be protracted, for sequalae such as diabetic ketoacidosis, euglycemic diabetic ketoacidosis, or hepatic lipidosis.
- Cats should be screened for urinary tract infections and treated, if indicated, when initiating Bexacat. Treatment with Bexacat may increase the risk for urinary tract infections (see Adverse Reactions). Cats treated with Bexacat should be monitored for urinary tract infections and treated promptly. Consider discontinuation of Bexacat in cats with recurrent urinary tract infections.
- Bexacat may cause increased serum calcium concentrations. Bexacat should be discontinued in cats with persistent increases in serum total calcium or ionized calcium because of increased risk of forming calcium containing uroliths (see Adverse Reactions).
- Long term use of Bexacat may increase the risk of urothelial carcinoma (see Adverse Reactions).
- Keep Bexacat in a secure location out of reach of dogs, cats, and other animals to prevent accidental ingestion or overdose.

PRECAUTIONS

- Bexacat should be discontinued in cats who develop diarrhea unresponsive to conventional therapy.
- Consider temporary discontinuation of Bexacat in cats during times of decreased caloric intake, such as surgery or decreased appetite, as administration of Bexacat in these cats may increase the risk of diabetic ketoacidosis or hepatic lipidosis.
- The osmotic diuretic effects of Bexacat may contribute to inappropriate urination in some cats (see Adverse Reactions).
- Polyphagia as a compensatory response to caloric wasting from glucosuria may persist in up to 80% of cats, despite evidence of adequate glycemic control, and may lead to progressive weight gain.
- Approximately 20-30% of cats may have persistent polyuria and/or polydipsia secondary to Bexacat-induced osmotic diuresis and may be a risk factor for dehydration-associated diabetic ketoacidosis.
- The concurrent use of volume depleting drugs in cats treated with Bexacat has not been evaluated.
- The safety of Bexacat in breeding, pregnant, and lactating cats has not been evaluated.

ADVERSE REACTIONS

Field Study

Eighty-four cats with newly diagnosed diabetes mellitus were enrolled in a 180-day multicenter field effectiveness and safety study. Safety data were evaluated in 84 cats treated with at least one dose of Bexacat. All cats received one tablet, once daily, regardless of body weight or blood glucose level. Seventy-two of the 84 enrolled cats completed the study. The most common adverse reactions included elevated blood urea nitrogen (BUN), vomiting, elevated urine specific gravity (USG), elevated serum fPL, diarrhea, anorexia, lethargy, and dehydration. The adverse reactions seen during the field study are summarized in Table 1 below.

Table 1. Adverse Reactions (n=84)
Adverse Reaction | Number (%)
Elevated BUN* | 46 (54.8)
Vomiting | 42 (50.0)
Elevated USG† | 33 (39.3)
Elevated fPL‡ | 33 (39.3)
Diarrhea | 32 (38.1)
Anorexia | 31 (37.0)
Lethargy | 17 (20.2)
Dehydration | 16 (19.0)
Elevated symmetrical dimethylarginine (SDMA) | 13 (15.5)
Weight loss | 13 (15.5)
Urinary tract infection | 12 (14.3)
Elevated ALT and/or AST§ | 11 (13.1)
Hypercalcemia | 8 (9.5)
Behavioral changes** | 6 (7.1)
Proteinuria | 5 (6.0)
Elevated creatinine | 4 (4.8)
Elevated creatine kinase | 4 (4.8)
Inappropriate urination | 4 (4.8)
Death | 3 (3.6)
Diabetic ketoacidosis | 3 (3.6)
Pancreatitis | 3 (3.6)
Euglycemic diabetic ketoacidosis | 2 (2.4)
Hepatic lipidosis | 2 (2.4)
Elevated alkaline phosphatase | 2 (2.4)
Elevated total bilirubin | 2 (2.4)
Constipation | 2 (2.4)
* Most cats had elevations < 1.5 times the upper limit of normal (ULN).
† Elevations were predominantly attributable to dehydration and/or glucosuria.
‡ Most cats had one or more isolated elevations, followed by a return to previous values.
§ Of nine cats with elevations ≥ 1.5X ULN, 2 cats developed diabetic ketoacidosis and were transitioned to insulin. One cat developed diabetic ketoacidosis and hepatic lipidosis resulting in death (euthanasia). One cat developed anemia, progressive weight loss and fPL elevations resulting in death.
** Observations included hiding, agitation, aggression, vocalization, and anxious behavior.

Nine serious adverse reactions associated with Bexacat administration occurred during the study, including three cats who died or were euthanized. Of the three cats who died or were euthanized, two cats became clinically ill within 5 doses of Bexacat administration (range 3 to 5 doses). One cat with euglycemic diabetic ketoacidosis and hepatic lipidosis was euthanized due to further deterioration of its clinical condition, despite supportive treatment. One cat demonstrating anorexia, lethargy, dehydration, azotemia, and hypokalemia was euthanized without supportive treatment. One cat, who demonstrated a lack of effectiveness, anemia and hepatic lipidosis died on Day 77 despite supportive treatment and additional diagnostics. Six of the nine cats had serious adverse reactions that did not result in death or euthanasia. Five cats were treated for their clinical conditions and transitioned to insulin. Serious adverse reactions in these cats were associated with the following conditions (number of cats): euglycemic diabetic ketoacidosis (1); lack of effectiveness, diabetic ketoacidosis, elevated liver parameters (1); diabetic ketoacidosis (1); diabetic ketoacidosis and pyelonephritis (1); and lack of effectiveness, weight loss, dehydration (1). One cat with constipation and pancreatitis received supportive treatment and remained on Bexacat (bexagliflozin tablets).

Pilot Field Study

Eighty-nine cats with newly diagnosed diabetes mellitus were enrolled in a 56-day multicenter pilot field effectiveness and safety study, with continued use for up to 180 days. All cats received one tablet, once daily, regardless of body weight or blood glucose level. Safety data were evaluated for all 89 cats treated with at least one dose of bexagliflozin. The most common adverse reactions included elevated blood urea nitrogen (BUN), elevated urine specific gravity (USG), elevated serum feline pancreas-specific lipase, vomiting, diarrhea/loose stool, hyporexia/anorexia, lethargy, elevated serum alanine aminotransferase (ALT) and/or aspartate aminotransferase (AST), and urinary tract infections. The adverse reactions seen in the pilot study are summarized in Table 2 below.

Table 2. Adverse Reactions (n=89)
Adverse Reaction | Number (%)
Elevated BUN* | 51 (57.3)
Elevated USG† | 43 (48.3)
Elevated fPL‡ | 39 (43.8)
Vomiting | 39 (43.8)
Diarrhea/Loose Stool | 29 (32.6)
Hyporexia/Anorexia | 28 (31.4)
Lethargy | 16 (18.0)
Elevated ALT and/or AST§ | 13 (14.6)
Urinary tract infection | 13 (14.6)
Dehydration | 10 (11.2)
Elevated symmetrical dimethylarginine (SDMA) | 10 (11.2)
Behavioral changes** | 9 (10.1)
Ketosis/Ketonuria | 8 (9.0)
Weight loss | 8 (9.0)
Proteinuria | 8 (9.0)
Pancreatitis | 7 (7.9)
Death | 6 (6.7)
Anemia | 6 (6.7)
Hepatopathy | 6 (6.7)
Hypercalcemia | 4 (4.5)
Elevated creatine kinase | 4 (4.5)
Inappropriate urination | 4 (4.5)
Peritonitis | 3 (3.4)
Constipation | 3 (3.4)
Elevated creatinine | 2 (2.2)
Euglycemic diabetic ketoacidosis | 2 (2.2)
Diabetic ketoacidosis | 2 (2.2)
Hemolytic anemia | 2 (2.2)
Elevated total bilirubin | 2 (2.2)
* Most cats had elevations ≤ 1.5X upper limit of normal (ULN).
† Elevations were predominantly attributable to dehydration and/or glucosuria.
‡ Most cats had one or more isolated elevations, followed by a return to previous values.
§ Most elevations were ≤ 2X ULN. One cat had marked ALT and AST (9X and 6X upper limit of normal, respectively) elevations on Day 28. Following discontinuation of bexagliflozin, the liver enzymes decreased within 24 hours and returned to within reference range in 10 days.
** Observations included hiding, hyperactivity, vocalization, and abnormal behavior.

Twenty cats (22%) had at least one blood glucose value < 65 mg/dL recorded during 8-hour blood glucose curves. No clinical signs of hypoglycemia were observed and bexagliflozin dosing was not adjusted in any cat due to documented hypoglycemia. Nine serious adverse reactions associated with bexagliflozin administration occurred during the study, including six cats who died or were euthanized. Of the six cats who died or were euthanized, five became clinically ill within receiving 5 doses of bexagliflozin (range 1 to 5 doses). Four of the cats were euthanized due to further deterioration of their clinical condition despite supportive treatment. One cat died despite supportive treatment. Deaths were associated with the following conditions (number of cats): necrotizing pancreatitis and pancreatic abscess (1), pancreatitis and hepatic lipidosis (1), euglycemic diabetic ketoacidosis and severe hepatic lipidosis (1), pancreatitis and hepatic abscesses (1), diabetic ketoacidosis (1), and persistent polyuria and polydipsia and quality of life concerns (1).

Three of nine serious adverse reactions that did not result in death or euthanasia included the following (number of cats): acute hepatocellular injury (1), immune-mediated hemolytic anemia (1), and euglycemic diabetic ketoacidosis with concurrent pancreatitis and hepatopathy (1). Two cats with serious adverse reactions demonstrated persistent bexagliflozin blood plasma levels and elimination half-lives after discontinuation of bexagliflozin. One cat with renal and liver values within the reference range at screening was euthanized due to a continued decline in clinical condition despite treatment for euglycemic diabetic ketoacidosis and severe hepatic lipidosis. The second cat, noted to have IRIS (International Renal Interest Society) stage II renal disease and liver values within the reference range at screening, recovered following treatment for marked liver enzyme elevations above the reference range on Day 28.

Extended Use Field Study

One hundred twenty-five cats with diabetes mellitus that had previously completed a bexagliflozin field study were enrolled in a multicenter extended use field study. Cats were enrolled in the study for a range of 7 to 1064 days, with a mean of 329 days. Safety data were evaluated for all 125 cats treated with at least one dose of Bexacat (bexagliflozin tablets). All cats received one tablet, once daily, regardless of body weight or blood glucose level. Forty-nine of the 125 enrolled cats were withdrawn from the study due to adverse reactions, serious adverse reactions, death/euthanasia, lack of effectiveness, suspected diabetic remission, withdrawal of owner consent, or lost to follow up. The most common adverse reactions were similar to those noted in the previous field studies and included elevated USG (35.2%), vomiting (27.2%), elevated fPL (26.4%), anorexia (24.0%), diarrhea (22.4%), urinary tract infections (17.6%), lethargy (16.8%), and death (16.0%).

Twenty serious adverse reactions associated with Bexacat administration occurred during the study, all resulting in death or euthanasia. Clinical signs of hypoglycemia were observed in two of these cats. Deaths were associated with the following conditions (number of cats), with some cats experiencing multiple comorbidities (necropsy was not granted in all cases): euglycemic diabetic ketoacidosis (8); diabetic ketoacidosis (4); hepatic lipidosis (5); pancreatic necrosis/peripancreatic fat saponification (3); urothelial carcinoma (2); hypercalcemia, recurrent calcium containing cystic calculi (1); lack of effectiveness, weight loss, anorexia (1); lethargy, weight loss, pallor (1); chronic renal disease, glomerulonephritis (1); chronic enteropathy (1); hypoglycemia, possible pancreatitis (1).

CONTACT INFORMATION

To report suspected adverse events, for technical assistance, or to obtain a copy of the Safety Data Sheet (SDS), contact Elanco US Inc at 1-888-545-5973.

For additional information about reporting adverse drug experiences for animal drugs, contact FDA at 1-888-FDA-VETS or http://www.fda.gov/reportanimalae

INFORMATION FOR CAT OWNERS

Owners should be given the Client Information Sheet to read before Bexacat is administered. Owners should be advised to discontinue Bexacat and contact a veterinarian immediately if their cat develops anorexia, lethargy, vomiting, diarrhea, or weakness.

CLINICAL PHARMACOLOGY

Mechanism of Action

Bexagliflozin is an inhibitor of sodium-glucose cotransporter 2 (SGLT2), the renal transporter responsible for reabsorption of glucose from the glomerular filtrate back into the circulation. By inhibiting SGLT2, bexagliflozin reduces renal reabsorption of filtered glucose and lowers the renal threshold for glucose, thereby increasing urinary glucose excretion.

Pharmacokinetics

In a laboratory pilot study conducted to determine the prandial state of maximum exposure, systemic exposure for bexagliflozin was greater in the fasted state than in the fed state by 82% for the mean maximum observed plasma concentration (Cmax), and by 54% for the mean area under the plasma concentration versus time curve (AUC) from dosing (time 0) to the last quantifiable concentration (AUC0-last), respectively.

In a well-controlled margin of safety study (see Target Animal Safety), mean Cmax was approximately dose-proportional over a dosage range of 5 mg/kg (1X) to 25 mg/kg (5X). Mean AUC from time 0 to 24 hours exposure was approximately dose-proportional over a dosage range of 5 to 15 mg/kg, but more than dose-proportional at 15 to 25 mg/kg. An increase in exposure (AUC0-24 and Cmax), was observed in female cats compared to male cats on all evaluation days. Median time to reach peak plasma concentration (Tmax) was approximately 0.5 hours (range 0.5 to 2 hours) and mean half-life (T1/2) was approximately 5 hours across all dose groups. There was no accumulation of bexagliflozin following daily dosing of 5, 15, and 25 mg/kg in healthy non-diabetic cats. However, field studies showed that some diabetic cats had persistent bexagliflozin blood levels after discontinuation of the drug, which may be related to a decrease in liver function in some cats (see Animal Safety Warnings)

EFFECTIVENESS

Field Study

Eighty-four cats diagnosed with diabetes mellitus were enrolled in a 180-day multicenter field effectiveness and safety study. Enrolled cats included purebreds and mixed breeds, ranging in age from 3 to 19 years, and weighing between 7.3 to 24.3 lbs (3.3 to 11.3 kg). Cats received one tablet, once daily, regardless of body weight or blood glucose level. Treatment success was defined as improvement in at least one blood glucose variable (blood glucose curve mean or fructosamine) and improvement in at least one clinical sign of diabetes mellitus (polyuria, polydipsia, polyphagia, or body weight [weight gain or no weight loss]).

Of 77 cats included in the effectiveness-evaluable population:

- 64 cats (83.1%) were considered a treatment success on Day 56.
- The lower bound two-sided 90% confidence interval was 74.5%. Effectiveness was demonstrated if the lower bound of the confidence interval was > 66%.
- Mean blood glucose curve mean decreased from 284 mg/dL on Day 0 to 143 mg/dL on Day 56.
- Mean fructosamine levels decreased from 544 µmol/L prior to Day 0 to 295 µmol/L on Day 56.
- Improvements in the clinical signs of polyuria, polydipsia, polyphagia, and body weight on Day 56 were observed in 53 (68.8%), 57 (74.0%), 44 (57.1%), and 42 (54.6%) cats, respectively.
- 66 cats (85.7%) completed the 180-day study.

Pilot Field Study

Eighty-nine cats diagnosed with diabetes mellitus were enrolled in a 56-day, multicenter pilot field effectiveness and safety study with continued use for up to 180 days. Enrolled cats included purebreds and mixed breeds, ranging in age from 3 to 17 years and weighing 6.4 to 22.9 lbs (2.9 to 10.4 kg). Cats received one tablet, once daily, regardless of weight. Treatment success was defined as improvement in at least one blood glucose variable (blood glucose curve mean or fructosamine) and improvement in at least one clinical sign of diabetes mellitus (polyuria, polydipsia, polyphagia, or body weight [weight gain or no weight loss]). Of the 72 cats included in the effectiveness-evaluable population, 58 (80.6%) were considered treatment successes on Day 56

TARGET ANIMAL SAFETY

In a well-controlled laboratory margin of safety study, Bexacat was administered orally to 28 fasted, healthy, lean, intact adult cats at doses of at least 1X (8 cats), 3X (8 cats), and 5X (12 cats) the maximum exposure dose (5 mg/kg) once daily for 26 weeks. The control group (8 cats) was sham dosed. The maximum exposure dose (5 mg/kg) was based on the assessment that the minimum weight of an eligible cat with diabetes mellitus is approximately 3 kg. Polyuria, glucosuria (with a corresponding increase in food consumption), loose stools and diarrhea, and ketonuria were reported more frequently in cats that received Bexacat than in control cats. There were drug-related clinically insignificant increases in calcium, magnesium, and cholesterol levels, and decreases in creatinine and amylase levels, and blood pressure and heart rate values. Gross necropsy demonstrated treatment-related observations of mild, diffuse zonal patterns in the liver. One cat with the observed zonal pattern had mild elevations of alanine aminotransferase (ALT) and aspartate aminotransferase (AST), and a histopathological observation of minimal, multifocal necrosis in the liver. The histopathological finding did not correspond to the zonal patterns observed grossly. There were no clinically relevant, drug-related effects on hematology and coagulation parameters and organ weight values

STORAGE CONDITIONS

Bexacat should be stored at room temperature 68 to 77 ˚F (20 to 25 °C)

HOW SUPPLIED

Flavored tablet each containing 15 mg bexagliflozin; 30 or 90 tablets per bottle.
Approved by FDA under NADA # 141-566
Manufactured for: Elanco US Inc, Greenfield, IN 46140
Bexacat, Elanco and the diagonal bar logo are trademarks of Elanco or its affiliates.
© 2022 Elanco or its affiliates

September 2022
PA103742

Client Information

ElancoTM

BexacatTM
(bexagliflozin tablets)
15 mg flavored tablets

Client Information Sheet

The Client Information Sheet contains important information about Bexacat. You should read this information before you start giving Bexacat to your cat and review it each time the prescription is refilled as there may be new information. This sheet is provided only as a summary and does not take the place of instructions from your veterinarian. Talk with your veterinarian if you do not understand any of this information or if you want to know more about Bexacat.

What is Bexacat?

Bexacat is a drug used to lower the amount of glucose (sugar) in the blood of otherwise healthy cats with diabetes mellitus not previously treated with insulin. Bexacat causes sugar to be passed out in the urine by preventing the kidneys from pulling sugar back into the blood.

What is diabetes mellitus (commonly called diabetes)?

Diabetes is a disease that affects how your cat’s body uses the sugar in its blood. Sugar is an important source of energy for the cells in your cat’s body. Cats with diabetes have high blood sugar because the sugar cannot get into the cells to be used for energy. Insulin helps sugar get into your cat’s cells for energy. Cats with diabetes may show an increase in thirst, hunger, and urination; weight loss; and/or weakness in the back legs.

Cats may have diabetes because, although they make enough insulin, their cells do not react to the insulin like they should (insulin resistant) or they do not make enough insulin and need to be given insulin for the cells to work the right way (insulin dependent). Some cats may begin as insulin resistant but may slowly become insulin dependent over time. Cats who are insulin dependent should not be treated with Bexacat because it may cause serious, sometimes fatal, side effects.

How does my veterinarian know if my cat is making enough insulin?

There is no test available for your veterinarian to know if your cat makes enough insulin or not. Based on your cat’s history and overall health, your veterinarian has decided Bexacat should be used to treat your cat’s diabetes.

What are some of the possible side effects of Bexacat?

Serious side effects have occurred, with or without warning, and have sometimes led to death in cats treated with Bexacat. Serious side effects may require your cat to be hospitalized and to be given specific treatments, including insulin. The most common side effects include vomiting, diarrhea or runny stools, less interest in food or not eating, lack of energy, and dehydration. Regular check-ups by your veterinarian are needed to monitor for side effects and to tell if your cat’s blood sugar is responding to Bexacat as expected.

STOP BEXACAT IMMEDIATELY AND CONTACT YOUR VETERINARIAN IF YOU NOTICE ANY OF THE FOLLOWING CHANGES OR SIDE EFFECTS IN YOUR CAT:

- Less interest in food or not eating
- Lack of energy or change in normal activity (for example, hiding or decreased grooming)
- Vomiting or diarrhea
- Weakness, difficulty walking or standing

What should I tell my veterinarian about my cat before starting Bexacat?

- Tell your veterinarian if your cat has ever been treated with insulin, and about any medications your cat is taking, including prescription drugs and over-the-counter medications.
- Tell your veterinarian about your cat’s past and present medical conditions, including a previous diagnosis of diabetes, diabetic ketoacidosis (a buildup of acids in the blood), hepatic lipidosis (fatty liver), pancreatitis (inflammation of the pancreas), or urinary tract infections.
- Tell your veterinarian if your cat has any planned procedures that involve anesthesia, such as surgery or dentistry.

How will Bexacat affect my cat?

You may see a decrease in the amount of thirst, urine, and hunger in your cat, and your cat may gain weight.

How do I give Bexacat to my cat?

Give one tablet of Bexacat to your cat by mouth once daily. If you miss giving a tablet of Bexacat, give it as soon as you remember on the same day. Then continue giving Bexacat on your regular schedule. If you accidentally give your cat more than one tablet of Bexacat on the same day, contact your veterinarian if you see any side effects. If no side effects are seen, keep giving Bexacat on your regular schedule. Do not skip a dose.

To report side effects in your cat, call Elanco US Inc at 1-888-545-5973. For additional information about reporting side effects, contact FDA at 1-888-FDA-VETS or http://www.fda.gov/reportanimalae.

Approved by FDA under NADA # 141-566

September 2022

Bexacat, Elanco and the diagonal bar logo are trademarks of Elanco or its affiliates.

© 2022 Elanco or its affiliates

PA103742B

PRINCIPAL DISPLAY PANEL

30 tablets

ElancoTM

BexacatTM
(bexagliflozin tablets)

15 mg flavored tablets

For oral use in cats only

Sodium-glucose
cotransporter 2
(SGLT2) inhibitor

CAUTION: Federal law restricts this drug
to use by or on the order of a licensed veterinarian.

WARNING: Due to serious animal
safety concerns, read the entire
package insert before using this drug,
including the complete boxed warning.

Bexacat is indicated to improve glycemic control
in otherwise healthy cats with diabetes mellitus
not previously treated with insulin.

30 tablets

BexacatTM
(bexagliflozin tablets)

15 mg flavored tablets

For oral use in cats only

WARNING: Due to serious animal
safety concerns, read the entire
package insert before using this drug,
including the complete boxed warning.

CAUTION: Federal law restricts
this drug to use by or on the
order of a licensed veterinarian.

Sodium-glucose cotransporter 2
(SGLT2) inhibitor

Provide the Client Information Sheet to
owners before administering Bexacat.

Approved by FDA under
NADA # 141-566

90 tablets

ElancoTM

BexacatTM
(bexagliflozin tablets)

15 mg flavored tablets

For oral use in cats only

Sodium-glucose
cotransporter 2
(SGLT2) inhibitor

CAUTION: Federal law restricts this drug
to use by or on the order of a licensed veterinarian.

WARNING: Due to serious animal
safety concerns, read the entire
package insert before using this drug,
including the complete boxed warning.

Bexacat is indicated to improve glycemic
control in otherwise healthy cats with diabetes
mellitus not previously treated with insulin.

90 tablets

Elanco

BexacatTM
(bexagliflozin tablets)

15 mg flavored tablets

For oral use in cats only

WARNING: Due to serious
animal safety concerns, read
the entire package insert before
using this drug, including the
complete boxed warning.

Bexacat is indicated to improve glycemic
control in otherwise healthy cats with diabetes
mellitus not previously treated with insulin.

CAUTION: Federal law
restricts this drug to use
by or on the order of a
licensed veterinarian.

Sodium-glucose
cotransporter 2
(SGLT2) inhibitor

Provide the Client Information
Sheet to owners before
administering Bexacat.

Approved by FDA under
NADA # 141-566